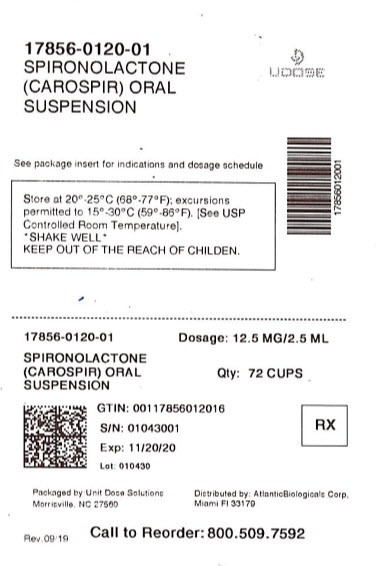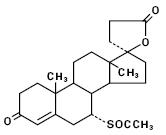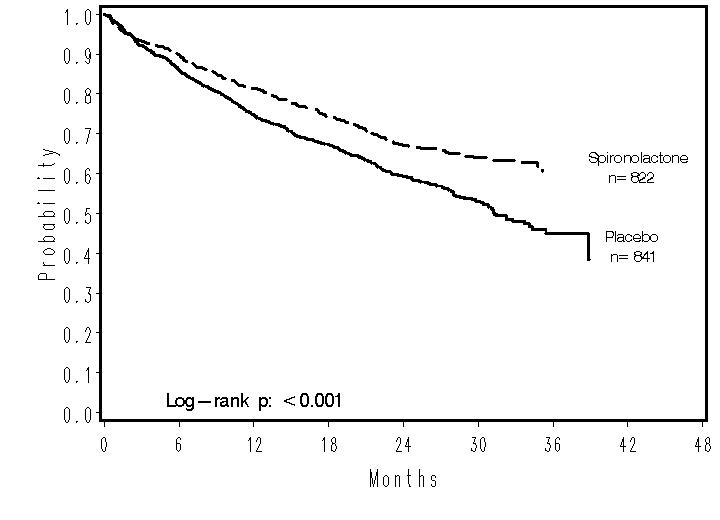 DRUG LABEL: CaroSpir
NDC: 17856-0120 | Form: Suspension
Manufacturer: ATLANTIC BIOLOGICALS CORP.
Category: prescription | Type: HUMAN PRESCRIPTION DRUG LABEL
Date: 20240412

ACTIVE INGREDIENTS: spironolactone 25 mg/5 mL
INACTIVE INGREDIENTS: xanthan gum; dimethicone; sorbic acid; potassium sorbate; saccharin sodium; anhydrous citric acid; trisodium citrate dihydrate; ammonium glycyrrhizate; glycerin; water

HIGHLIGHTS OF PRESCRIBING INFORMATION

These highlights do not include all the information needed to use CAROSPIR® safely and effectively. See full prescribing information for CAROSPIR®.
CAROSPIR® (spironolactone) Oral Suspension, for oral use
Initial U.S. Approval: 1960

1 INDICATIONS AND USAGE

CAROSPIR is an antagonist of aldosterone indicated for:

- the treatment of NYHA Class III-IV heart failure and reduced ejection fraction to increase survival, manage edema, and to reduce the need for hospitalization for heart failure (1.1)
- use as an add-on therapy for the treatment of hypertension, to lower blood pressure. Lowering blood pressure reduces the risk of fatal and nonfatal cardiovascular events, primarily strokes and myocardial infarctions (1.2)
- the management of edema in adult cirrhotic patients when edema is not responsive to fluid and sodium restrictions (1.3)

2 DOSAGE AND ADMINISTRATION

- CAROSPIR is not therapeutically equivalent to Aldactone (2.1)
- Heart Failure: Initiate treatment at 20 mg once daily. (2.2)
- Hypertension: Initiate treatment at 20 to 75 mg daily in either single or divided doses (2.3)
- Edema associated with Hepatic Cirrhosis: Initiate therapy in a hospital setting and titrate slowly. The initial recommended daily dose is 75 mg in either single or divided doses (2.4)

3 DOSAGE FORMS AND STRENGTHS

Oral suspension, 25 mg/5 mL

4 CONTRAINDICATIONS

CAROSPIR is contraindicated in patients with (4)

- Hyperkalemia
- Addison’s disease
- Concomitant use of eplerenone

5 WARNINGS AND PRECAUTIONS

- Hyperkalemia: Monitor serum potassium within one week of initiation and regularly thereafter (5.1)
- Hypotension and Worsening Renal Function: Monitor volume status and renal function periodically (5.2)
- Electrolyte and Metabolic Abnormalities: Monitor serum electrolytes, uric acid and blood glucose periodically (5.3)
- Gynecomastia: CAROSPIR can cause gynecomastia (5.4)

6 ADVERSE REACTIONS

The most common adverse reaction (incidence > 5%) with CAROSPIR treatment is gynecomastia (6)

To report SUSPECTED ADVERSE REACTIONS, contact CMP Pharma at 1-844-321-1443 or FDA at 1-800-FDA-1088 or www.fda.gov/medwatch.

7 DRUG INTERACTIONS

- Agents increasing serum potassium: Concomitant administration can lead to hyperkalemia (5.1, 7.1)
- Lithium: Increased risk of lithium toxicity (7.2)
- NSAIDs: May reduce the diuretic, natriuretic and antihypertensive effect of CAROSPIR (7.3)
- Digoxin: CAROSPIR can interfere with radioimmunologic assays of digoxin exposure (7.4)
- Cholestyramine: Hyperkalemic metabolic acidosis has been reported with concomitant use (7.5)
- Acetylsalicylic Acid (ASA): ASA may reduce the efficacy of spironolactone (7.6)

8 USE IN SPECIFIC POPULATIONS

- Pregnancy; Based on animal data, spironolactone may affect sex differentiation of the male during embryogenesis (8.1)

FULL PRESCRIBING INFORMATION

1 INDICATIONS AND USAGE

CAROSPIR (spironolactone) is indicated in the management of:

1.1 Heart Failure

CAROSPIR is indicated for treatment of NYHA Class III-IV heart failure and reduced ejection fraction to increase survival, manage edema, and to reduce the need for hospitalization for heart failure.

CAROSPIR is usually administered in conjunction with other heart failure therapies.

1.2 Hypertension

CAROSPIR is indicated as an add-on therapy for the treatment of hypertension, to lower blood pressure in adult patients who are not adequately controlled on other agents. Lowering blood pressure reduces the risk of fatal and nonfatal cardiovascular events, primarily strokes and myocardial infarctions. These benefits have been seen in controlled trials of antihypertensive drugs from a wide variety of pharmacologic classes.

Control of high blood pressure should be part of comprehensive cardiovascular risk management, including, as appropriate, lipid control, diabetes management, antithrombotic therapy, smoking cessation, exercise, and limited sodium intake. Many patients will require more than one drug to achieve blood pressure goals. For specific advice on goals and management, see published guidelines, such as those of the National High Blood Pressure Education Program’s Joint National Committee on Prevention, Detection, Evaluation, and Treatment of High Blood Pressure (JNC).

Numerous antihypertensive drugs, from a variety of pharmacologic classes and with different mechanisms of action, have been shown in randomized controlled trials to reduce cardiovascular morbidity and mortality, and it can be concluded that it is blood pressure reduction, and not some other pharmacologic property of the drugs, that is largely responsible for those benefits. The largest and most consistent cardiovascular outcome benefit has been a reduction in the risk of stroke, but reductions in myocardial infarction and cardiovascular mortality also have been seen regularly. Elevated systolic or diastolic pressure causes increased cardiovascular risk, and the absolute risk increase per mmHg is greater at higher blood pressures, so that even modest reductions of severe hypertension can provide substantial benefit. Relative risk reduction from blood pressure reduction is similar across populations with varying absolute risk, so the absolute benefit is greater in patients who are at higher risk independent of their hypertension (for example, patients with diabetes or hyperlipidemia), and such patients would be expected to benefit from more aggressive treatment to a lower blood pressure goal.

Some antihypertensive drugs have smaller blood pressure effects (as monotherapy) in black patients, and many antihypertensive drugs have additional approved indications and effects (e.g. on angina, heart failure, or diabetic kidney disease). These considerations may guide selection of therapy.

1.3 Edema caused by Cirrhosis

CAROSPIR is indicated for the management of edema in adult cirrhotic patients when edema is not responsive to fluid and sodium restriction.

2 DOSAGE AND ADMINISTRATION

2.1 General Considerations

CAROSPIR is not therapeutically equivalent to Aldactone. Follow dosing instructions given here. In patients requiring a dose greater than 100 mg, use another formulation. Doses of the suspension greater than 100 mg may result in spironolactone concentrations higher than expected [see Clinical Pharmacology (12.3)].

CAROSPIR can be taken with or without food, but should be taken consistently with respect to food [see Clinical Pharmacology (12.3)].

2.2 Treatment of Heart Failure

In patients with serum potassium ≤5.0 mEq/L and eGFR >50 mL/min/1.73m^2, initiate treatment at 20 mg (4 mL) once daily. Patients who tolerate 20 mg (4 mL) once daily may have their dosage increased to 37.5 mg (7.5 mL) once daily as clinically indicated. Patients who develop hyperkalemia on 20 mg (4 mL) once daily may have their dosage reduced to 20 mg (4 mL) every other day [see Warning and Precautions 5.1)]. In patients with an eGFR between 30 and 50 mL/min/1.73m^2, consider initiating treatment at 10 mg (2 mL) because of the risk of hyperkalemia [see Use in Specific Populations (8.6)].

2.3 Treatment of Essential Hypertension

The recommended initial daily dose is 20 mg (4 mL) to 75 mg (15 mL) administered in either single or divided doses. Dosage can be titrated at two-week intervals. Doses >75 mg/day generally do not provide additional reductions in blood pressure.

2.4 Treatment of Edema associated with Hepatic Cirrhosis

In patients with cirrhosis, initiate therapy in a hospital setting and titrate slowly [see Use in Specific Populations (8.6)] and Clinical Pharmacology (12.3)]. The recommended initial daily dose is 75 mg (15 mL) administered in either single or divided doses. In patients requiring titration above 100 mg, use another formulation [see Dosage and Administration (2.1)]. When given as the sole agent for diuresis, administer for at least five days before increasing dose to obtain desired effect.

3 DOSAGE FORMS AND STRENGTHS

Oral Suspension: 25 mg/5 mL (5 mg/mL); white to off-white, banana flavored.

4 CONTRAINDICATIONS

CAROSPIR is contraindicated for patients with the following conditions:

- Hyperkalemia
- Addison’s disease
- Concomitant use of eplerenone

5 WARNINGS AND PRECAUTIONS

5.1 Hyperkalemia

CAROSPIR can cause hyperkalemia. This risk is increased by impaired renal function or concomitant potassium supplementation, potassium-containing salt substitutes or drugs that increase potassium, such as angiotensin converting enzyme inhibitors and angiotensin receptor blockers [see Drug Interactions (7.1)].

Closer monitoring may be needed when CAROSPIR is given with other drugs that cause hyperkalemia or in patients with impaired renal function.

If hyperkalemia occurs, decrease the dose or discontinue CAROSPIR and treat hyperkalemia.

5.2 Hypotension and Worsening Renal Function

Excessive diuresis may cause symptomatic dehydration, hypotension and worsening renal function, particularly in salt-depleted patients or those taking angiotensin converting enzyme inhibitors and angiotensin II receptor blockers. Worsening of renal function can also occur with concomitant use of nephrotoxic drugs (e.g., aminoglycosides, cisplatin, and NSAIDs). Monitor volume status and renal function periodically.

5.3 Electrolyte and Metabolic Abnormalities

In addition to causing hyperkalemia, CAROSPIR can cause hyponatremia, hypomagnesemia, hypocalcemia, hypochloremic alkalosis, and hyperglycemia. Asymptomatic hyperuricemia can occur and rarely gout is precipitated. Monitor serum electrolytes, uric acid and blood glucose periodically.

5.4 Gynecomastia

CAROSPIR can cause gynecomastia. In RALES, patients with heart failure treated with a mean dose of 26 mg of spironolactone once daily, about 9% of the male subjects developed gynecomastia. The risk of gynecomastia increases in a dose-dependent manner with an onset that varies widely from 1-2 months to over a year. Gynecomastia is usually reversible.

6 ADVERSE REACTIONS

The following clinically significant adverse reactions are described elsewhere in the labeling:

- Hyperkalemia [see Warnings and Precautions (5.1)]
- Hypotension and Worsening Renal Function [see Warnings and Precautions (5.2)]
- Electrolyte and Metabolic Abnormalities [see Warnings and Precautions (5.3)]
- Gynecomastia [see Warnings and Precautions (5.4)]
- Impaired neurological function/ coma in patients with hepatic impairment, cirrhosis and ascites [see Use in Specific Populations (8.7)]

The following adverse reactions associated with the use of spironolactone were identified in clinical trials or postmarketing reports. Because these reactions were reported voluntarily from a population of uncertain size, it is not always possible to estimate their frequency, reliably, or to establish a causal relationship to drug exposure.

Digestive: Gastric bleeding, ulceration, gastritis, diarrhea and cramping, nausea, vomiting.

Reproductive: Gynecomastia [see Warnings and Precautions (5.4)], decreased libido, inability to achieve or maintain erection, irregular menses or amenorrhea, postmenopausal bleeding, breast nad nipple pain.

Hematologic: Leukopenia (including agranulocytosis), thrombocytopenia.

Hypersensitivity: Fever, urticaria, maculopapular or erythematous cutaneous eruptions, anaphylactic reactions, vasculitis.

Metabolism: Hyperkalemia, electrolyte disturbances [see Warnings and Precautions (5.1, 5.3)], hyponatremia, hypovolemia.

Musculoskeletal: Leg cramps.

Nervous system /psychiatric: Lethargy, mental confusion, ataxia, dizziness, headache, drowsiness.

Liver / biliary: A very few cases of mixed cholestatic/hepatocellular toxicity, with one reported fatality, have been reported with spironolactone administration.

Renal: Renal dysfunction (including renal failure).

Skin: Stevens-Johnson Syndrome (SJS), toxic epidermal necrolysis (TEN), drug rash with eosinophilia and systemic symptoms (DRESS), alopecia, pruritis, chloasma.

7 DRUG INTERACTIONS

7.1 Drugs and Supplements Increasing Serum Potassium

Concomitant administration of CAROSPIR with potassium supplementation or drugs that can increase potassium may lead to severe hyperkalemia. In general, discontinue potassium supplementation in heart failure patients who start CAROSPIR [see Warnings and Precautions (5.1) and Clinical Pharmacology (12.3)]. Check serum potassium levels when ACE inhibitor or ARB therapy is altered in patients receiving CAROSPIR.

Examples of drugs that can increase potassium include:

- ACE inhibitors
- angiotensin receptor blockers
- aldosterone blockers
- non-steroidal anti-inflammatory drugs (NSAIDs)
- heparin and low molecular weight heparin
- trimethoprim

7.2 Lithium

Like other diuretics, CAROSPIR reduces the renal clearance of lithium, thus increasing the risk of lithium toxicity. Monitor lithium levels periodically when CAROSPIR is coadministered [see Clinical Pharmacology (12.3)].

7.3 Nonsteroidal Anti-Inflammatory Drugs (NSAIDs)

In some patients, the administration of an NSAID can reduce the diuretic, natriuretic, and antihypertensive effect of loop, potassium-sparing, and thiazide diuretics. Therefore, when CAROSPIR and NSAIDs are used concomitantly, monitor closely to determine if the desired effect of the diuretic is obtained [see Clinical Pharmacology (12.3)].

7.4 Digoxin

Spironolactone and its metabolites interfere with radioimmunoassays for digoxin and increase the apparent exposure to digoxin. It is unknown to what extent, if any, spironolactone may increase actual digoxin exposure. In patients taking concomitant digoxin, use an assay that does not interact with spironolactone. [see Clinical Pharmacology (12.3)].

7.5 Cholestyramine

Hyperkalemic metabolic acidosis has been reported in patients given spironolactone concurrently with cholestyramine.

7.6 Acetylsalicylic Acid

Acetylsalicylic acid may reduce the efficacy of spironolactone. Therefore, when CAROSPIR and acetylsalicylic acid are used concomitantly, CAROSPIR may need to be titrated to higher maintenance dose and the patient should be observed closely to determine if the desired effect is obtained [see Clinical Pharmacology (12.3)].

8 USE IN SPECIFIC POPULATIONS

8.1 Pregnancy

Risk Summary
Based on mechanism of action and findings in animal studies, spironolactone may affect sex differentiation of the male during embryogenesis [see Clinical Pharmacology (12.1)].. Rat embryofetal studies report feminization of male fetuses and endocrine dysfunction in females exposed to spironolactone in utero. Limited available data from published case reports and case series did not demonstrate an association of major malformations or other adverse pregnancy outcomes with spironolactone. There are risks to the mother and fetus associated with heart failure, cirrhosis and poorly controlled hypertension during pregnancy (see Clinical Considerations). Because of the potential risk to the male fetus due to anti-androgenic properties of spironolactone and animal data, avoid spironolactone in pregnant women or advise a pregnant woman of the potential risk to a male fetus.

The estimated background risk of major congenital anomalies and miscarriage for the indicated population is unknown. All pregnancies have a background risk of birth defect, loss or other adverse outcomes. In the U.S. general population, the estimated background risk of major congenital anomalies and miscarriage in the clinically recognized pregnancies is 2% to 4% and 15% to 20%, respectively.

Clinical Considerations
Disease-Associated Maternal and/or Embryo/Fetal Risk Pregnant women with congestive heart failure are at increased risk for preterm birth. Stroke volume and heart rate increase during pregnancy, increasing cardiac output, especially during the first trimester. Clinical classification of heart disease may worsen with pregnancy and lead to maternal death. Closely monitor pregnant patients for destabilization of their heart failure.

Pregnant women with symptomatic cirrhosis generally have poor outcomes including hepatic failure, variceal hemorrhage, preterm delivery, fetal growth restriction and maternal death. Outcomes are worse with coexisting esophageal varices. Pregnant women with cirrhosis of the liver should be carefully monitored and managed accordingly.

Hypertension in pregnancy increases the maternal risk for pre-eclampsia, gestational diabetes, premature delivery, and delivery complications (e.g., need for cesarean section, and post-partum hemorrhage). Hypertension increases the fetal risk for intrauterine growth restriction and intrauterine death.

Data
Animal Data
Teratology studies with spironolactone have been carried out in mice and rabbits at doses of up to 20 mg/kg/day. On a body surface area basis, this dose in the mouse is substantially below the maximum recommended human dose and, in the rabbit, approximates the maximum recommended human dose. No teratogenic or other embryo toxic effects were observed in mice, but the 20 mg/kg dose caused an increased rate of resorption and a lower number of live fetuses in rabbits. Because of its antiandrogenic activity and the requirement of testosterone for male morphogenesis, CAROSPIR may have the potential for adversely affecting sex differentiation of the male during embryogenesis. When administered to rats at 200 mg/kg/day, a dose 10 times the human dose of 200 mg/day, when based on body surface area, between gestation days 13 and 21 (late embryogenesis and fetal development), feminization of male fetuses was observed. Offspring exposed during late pregnancy to 50 and 100 mg/kg/day doses of spironolactone exhibited changes in the reproductive tract including dose-dependent decreases in weights of the ventral prostate and seminal vesicle in males, ovaries and uteri that were enlarged in females, and other indications of endocrine dysfunction, that persisted into adulthood. Spironolactone (CAROSPIR) has known endocrine effects in animals including progestational and antiandrogenic effects.

8.2 Lactation

Risk Summary
Spironolactone is not present in breastmilk; however, limited data from a lactating woman at 17 days postpartum reports the presence of the active metabolite, canrenone, in human breast milk in low amounts that are expected to be clinically inconsequential. In this case, there were no adverse effects reported for the breastfed infant after short term exposure to spironolactone; however, long term effects on a breastfed infant are unknown. There are no data on spironolactone effects on milk production. Consider the developmental and health benefits of breastfeeding along with the mother’s clinical need for spironolactone and any potential adverse effects on the breastfed child from spironolactone or from the underlying maternal condition.

8.4 Pediatric Use

Safety and effectiveness in pediatric patients have not been established.

8.5 Geriatric Use

CAROSPIR is substantially excreted by the kidney, and the risk of adverse reactions to this drug may be greater in patients with impaired renal function. Because elderly patients are more likely to have decreased renal function, monitor renal function.

8.6 Use in Renal Impairment

CAROSPIR is substantially excreted by the kidney, and the risk of adverse reactions to this drug may be greater in patients with impaired renal function. Patients with renal impairment are at increased risk of hyperkalemia. Monitor potassium closely.

8.7 Use in Hepatic Impairment

CAROSPIR can cause sudden alterations of fluid and electrolyte balance which may precipitate impaired neurological function, worsening hepatic encephalopathy and coma in patients with hepatic disease with cirrhosis and ascites. In these patients, initiate CAROSPIR in the hospital [see Dosage and Administration (2.4), and Clinical Pharmacology (12.3)].

Clearance of spironolactone and its metabolites is reduced in patients with cirrhosis. In patients with cirrhosis, start with lowest initial dose and titrate slowly [see Dosage and Administration (2.1, 2.4), and Clinical Pharmacology (12.3)].

10 OVERDOSAGE

The oral LD50 of spironolactone is greater than 1000 mg/kg in mice, rats, and rabbits.

Acute overdosage of CAROSPIR may be manifested by drowsiness, mental confusion, maculopapular or erythematous rash, nausea, vomiting, dizziness, or diarrhea. Rarely, instances of hyponatremia, hyperkalemia, or hepatic coma may occur in patients with severe liver disease, but these are unlikely due to acute overdosage. Hyperkalemia may occur, especially in patients with impaired renal function.

Treatment: Induce vomiting or evacuate the stomach by lavage. There is no specific antidote. Treatment is supportive to maintain hydration, electrolyte balance, and vital functions. Patients who have renal impairment may develop hyperkalemia. In such cases, discontinue CAROSPIR.

11 DESCRIPTION

CAROSPIR Oral Suspension contains 25 mg of the aldosterone antagonist spironolactone, 17-hydroxy-7α-mercapto-3-oxo-17α-pregn-4-ene-21- carboxylic acid γ-lactone acetate per 5 mL, which has the following structural formula:

Spironolactone is practically insoluble in water, soluble in alcohol, and freely soluble in benzene and in chloroform.

Inactive ingredients include sorbic acid, potassium sorbate, citric acid anhydrous, sodium citrate dihydrate, simethicone emulsion, saccharin sodium, xanthan gum, Magnasweet 110, glycerin, banana flavor, and purified water.

12 CLINICAL PHARMACOLOGY

12.1 Mechanism of Action

Spironolactone and its active metabolites are specific pharmacologic antagonists of aldosterone, acting primarily through competitive binding of receptors at the aldosterone-dependent sodium-potassium exchange site in the distal convoluted renal tubule. Spironolactone causes increased amounts of sodium and water to be excreted, while potassium is retained. Spironolactone acts both as a diuretic and as an antihypertensive drug by this mechanism. It may be given alone or with other diuretic agents that act more proximally in the renal tubule.

12.2 Pharmacodynamics

Aldosterone antagonist activity: Increased levels of the mineralocorticoid, aldosterone, are present in primary and secondary hyperaldosteronism. Edematous states in which secondary aldosteronism is usually involved include congestive heart failure, hepatic cirrhosis, and nephrotic syndrome. By competing with aldosterone for receptor sites, Spironolactone provides effective therapy for the edema and ascites in those conditions. Spironolactone counteracts secondary aldosteronism induced by the volume depletion and associated sodium loss caused by active diuretic therapy.

12.3 Pharmacokinetics

For an equivalent dose, CAROSPIR results in 15 to 37% higher serum concentration compared to Aldactone tablets. Information about the dose proportionality of spironolactone tablets is limited and, based on the results of studies comparing the suspension to tablets, doses of suspension higher than 100 mg might result in spironolactone concentrations that could be higher than expected.

Absorption
The peak plasma concentration (Cmax) of spironolactone is reached 0.5 to 1.5 hours after dosing in healthy volunteers; for the active metabolite canrenone, the Cmax is reached around 2.5 to 5 hours after dosing.

Effect of food: A high fat and high calorie meal (57% of the ~1000 kcal of the meal were from fat) increased the bioavailability of spironolactone (as measured by AUC) by approximately 90%. Patients should establish a routine pattern for taking CAROSPIR with regard to meals [see Dosage and Administration (2.1)].

Distribution
Spironolactone and its metabolites are more than 90% bound to plasma proteins.

Elimination
The half-life of spironolactone is approximately 1- 2 hour, and the half-life of canrenone, 7-α-(thiomethyl) spirolactone (TMS), and 6-ß-hydroxy-7-α-(thiomethyl) spirolactone (HTMS) ranged from 10 to 35 hours.

Metabolism:
Spironolactone is rapidly and extensively metabolized. Metabolites can be divided into two main categories: those in which sulfur of the parent molecule is removed (e.g., canrenone) and those in which the sulfur is retained (e.g., TMS and HTMS). In humans, the potencies of TMS and 7-α-thiospirolactone in reversing the effects of the synthetic mineralocorticoid, fludrocortisone, on urinary electrolyte composition were approximately a third relative to spironolactone. However, since the serum concentrations of these steroids were not determined, their incomplete absorption and/or first-pass metabolism could not be ruled out as a reason for their reduced in vivo activities.

Excretion:The metabolites are excreted primarily in the urine and secondarily in bile.

Specific Populations
The impact of age, sex, race/ethnicity, and renal impairment on the pharmacokinetics of spironolactone have not been specifically studied.

Patients with Hepatic Impairment: The terminal half-life of spironolactone has been reported to be increased in patients with cirrhotic ascites [see Use in Specific Populations (8.7)].

Drug Interaction Studies:
Drugs and Supplements Increasing Serum Potassium: Concomitant administration of CAROSPIR with potassium supplementation, salt substitutes containing potassium, a diet rich in potassium, or drugs that can increase potassium, including ACE inhibitors, angiotensin II antagonists, non-steroidal anti-inflammatory drugs (NSAIDs), heparin and low molecular weight heparin, may lead to severe hyperkalemia [see Warnings and Precautions (5.1)].

Lithium: CAROSPIR reduces the renal clearance of lithium, inducing a high risk of lithium toxicity [see Warnings and Precautions (5.1) and Drug Interactions (7.2)].

Nonsteroidal Anti-Inflammatory Drugs (NSAIDs): In some patients, the administration of an NSAID can reduce the diuretic, natriuretic, and antihypertensive effect of loop, potassium-sparing, and thiazide diuretics [see Drug Interactions (7.3)].

Acetylsalicylic acid: A single dose of 600 mg of acetylsalicylic acid inhibited the natriuretic effect of spironolactone, which was hypothesized be due to inhibition of tubular secretion of canrenone, causing decreased effectiveness of spironolactone [see Drug Interactions (7.6)].

13 NONCLINICAL TOXICOLOGY

13.1 Carcinogenesis, Mutagenesis, Impairment of Fertility

Carcinogenesis
Orally administered spironolactone has been shown to be a tumorigen in dietary administration studies performed in rats, with its proliferative effects manifested on endocrine organs and the liver. In an 18-month study using doses of about 50, 150, and 500 mg/kg/day, there were statistically significant increases in benign adenomas of the thyroid and testes and, in male rats, a dose-related increase in proliferative changes in the liver (including hepatocytomegaly and hyperplastic nodules). In a 24-month study in which the same strain of rat was administered doses of about 10, 30, 100, and 150 mg spironolactone/kg/day, the range of proliferative effects included significant increases in hepatocellular adenomas and testicular interstitial cell tumors in males, and significant increases in thyroid follicular cell adenomas and carcinomas in both sexes. There was also a statistically significant, but not dose-related, increase in benign uterine endometrial stromal polyps in females. No increased tumors were seen at doses of 100 mg/kg/day. This dose represents about 5-times the human recommended daily dose of 200 mg/day, when based on body surface area.

Mutagenesis
Neither spironolactone nor potassium canrenoate produced mutagenic effects in tests using bacteria or yeast. In the absence of metabolic activation, neither spironolactone nor potassium canrenoate has been shown to be mutagenic in mammalian tests in vitro. In the presence of metabolic activation, Spironolactone has been reported to be negative in some mammalian mutagenicity tests in vitro and inconclusive (but slightly positive) for mutagenicity in other mammalian tests in vitro. In the presence of metabolic activation, potassium canrenoate has been reported to test positive for mutagenicity in some mammalian tests in vitro, inconclusive in others, and negative in still others.

Impairment of Fertility
In a three-litter reproduction study in which female rats received dietary doses of 15 and 50 mg spironolactone/kg/day, there were no effects on mating and fertility, but there was a small increase in incidence of stillborn pups at 50 mg/kg/day. When injected into female rats (100 mg/kg/day for 7 days, i.p.), spironolactone was found to increase the length of the estrous cycle by prolonging diestrus during treatment and inducing constant diestrus during a two-week post-treatment observation period. These effects were associated with retarded ovarian follicle development and a reduction in circulating estrogen levels, which would be expected to impair mating, fertility, and fecundity. Spironolactone (100 mg/kg/day), administered i.p. to female mice during a two-week cohabitation period with untreated males, decreased the number of mated mice that conceived (effect shown to be caused by an inhibition of ovulation) and decreased the number of implanted embryos in those that became pregnant (effect shown to be caused by an inhibition of implantation), and at 200 mg/kg, also increased the latency period to mating.

14 CLINICAL STUDIES

14.1 Heart failure

The Randomized Aldactone Evaluation Study (RALES) was a placebo-controlled, double-blind study of the effect of spironolactone on mortality in patients with highly symptomatic heart failure and reduced ejection fraction. To be eligible to participate, patients had to have an ejection fraction of ≤35%, NYHA Class III-IV symptoms, and a history of NYHA class IV symptoms within the last 6 months before enrollment. Patients with a baseline serum creatinine of >2.5 mg/dL or a recent increase of 25% or with a baseline serum potassium of >5.0 mEq/L were excluded.

Follow-up visits and laboratory measurements (including serum potassium and creatinine) were performed every four weeks for the first 12 weeks, then every 3 months for the first year, and then every 6 months thereafter.

The RALES study was conducted with a formulation of spironolactone that is not therapeutically equivalent to CAROSPIR [see Dosage and Administration (2.1), and Clinical Pharmacology (12.3)]. The initial dose of spironolactone was 25 mg once daily. Patients who were intolerant of the initial dosage regimen had their dose decreased to one 25 mg tablet every other day at one to four weeks. Patients who were tolerant of one tablet daily at 8 weeks could have had their dose increased 50 mg daily at the discretion of the investigator. The mean daily dose at study end for the patients randomized to spironolactone was 26 mg.

1663 patients were randomized 1:1 to spironolactone or placebo. 87% of patients were white, 7% black, and 2% Asian. 73% were male and median age was 67. The median ejection fraction was 26%. 70% were NYHA class III and 29% class IV. The etiology of heart failure was ischemic in 55%, and non-ischemic in 45%. There was a history of myocardial infarction in 28%, of hypertension in 24%, and of diabetes in 22%. The median baseline serum creatinine was 1.2 mg/dL and the median baseline creatinine clearance was 57 mL/min.

At baseline, 100% of patients were taking loop diuretic and 95% were taking an ACE inhibitor. Other medications used at any time during the study included digoxin (78%), anticoagulants (58%), aspirin (43%), and beta-blockers (15%).

The primary endpoint for RALES was time to all-cause mortality. RALES was terminated early because of significant mortality benefit demonstrated during a planned interim analysis. Compared to placebo, spironolactone reduced the risk of death by 30% (p<0.001; 95% confidence interval 18% to 40%). Spironolactone also reduced the risk of hospitalization for cardiac causes (defined as worsening heart failure, angina, ventricular arrhythmias, or myocardial infarction) by 30% (p<0.001 95% confidence interval 18% to 41%).

The survival curves by treatment group are shown in Figure 1.

Figure 1. Survival by Treatment Group in RALES

Mortality hazard ratios for subgroups were studied. The favorable effect of spironolactone on mortality appeared similar for both genders and all age groups except patients younger than 55. There were too few non-whites in RALES to evaluate if the effects differ by race. Spironolactone’s benefit appeared greater in patients with low baseline serum potassium levels and less in patients with ejection fractions <0.2. These subgroup analyses must be interpreted cautiously.

14.2 Hypertension

Studies of the treatment of hypertension were conducted with a formulation of spironolactone that is not therapeutically equivalent to CAROSPIR [see Dosage and Administration (2.1), and Clinical Pharmacology (12.3)]. In a study in 24 patients with essential hypertension, of which only eight completed study assessments, the average BP systolic lowering was 10 mmHg and 20 mmHg for the 25 mg and 100 mg doses of spironolactone, respectively. Doses >100 mg/day generally do not provide additional reductions in blood pressure.

16 HOW SUPPLIED/STORAGE AND HANDLING

CAROSPIR (spironolactone) Oral Suspension 25 mg/5 mL is a white to off-white, opaque, banana-flavored suspension. It is available in a 118 mL bottle (NDC 46287-020-04) and a 473 mL bottle (NDC 46287-020-01).

Store at 20° to 25°C (68° to 77°F). Excursions permitted to 15° to 30°C (59° to 86°F) [See USP Controlled Room Temperature]. Shake well before use. Dispense in a tight container as defined in the USP.

17 PATIENT COUNSELING INFORMATION

- Advise patients to take CAROSPIR consistently with respect to food.
- Patients who receive CAROSPIR should avoid potassium supplements and foods containing high levels of potassium, including salt substitutes.
- Pregnancy: Advise a pregnant woman of the potential risk to a fetus. Advise females of reproductive potential to inform their prescriber of a known or suspected pregnancy [see Use in Specific Populations (8.1)].

DISTRIBUTED BY:

ATLANTIC BIOLOGICALS CORP.

20101 N.E 16th PLACE

MIAMI, FL 33179

PACKAGE LABEL

NDC 17856-0120-1

CaroSpir

Spironolactone Oral Suspension
2.5mL Cups 72

For Oral Use Only

Shake well before use

Rx Only